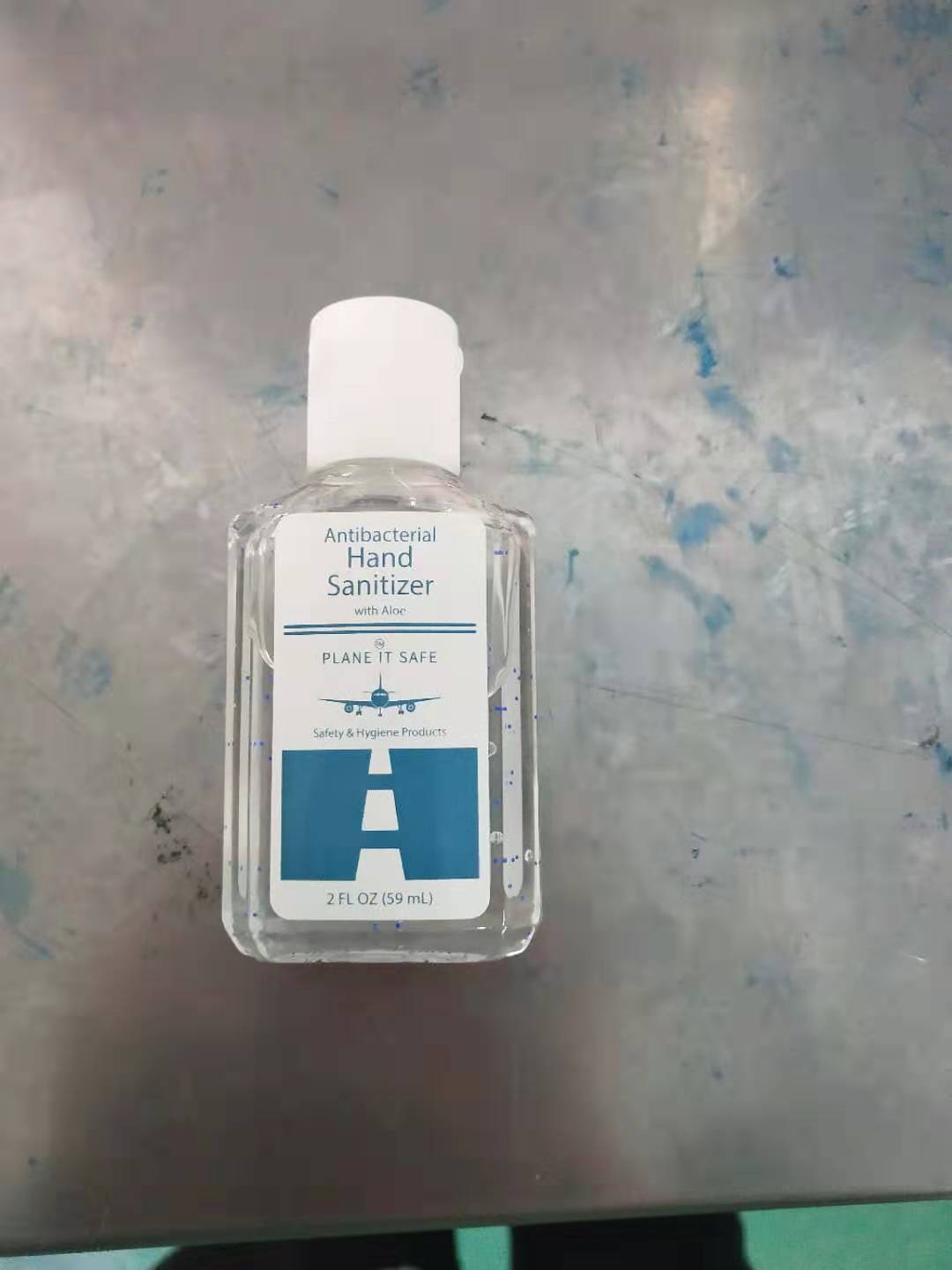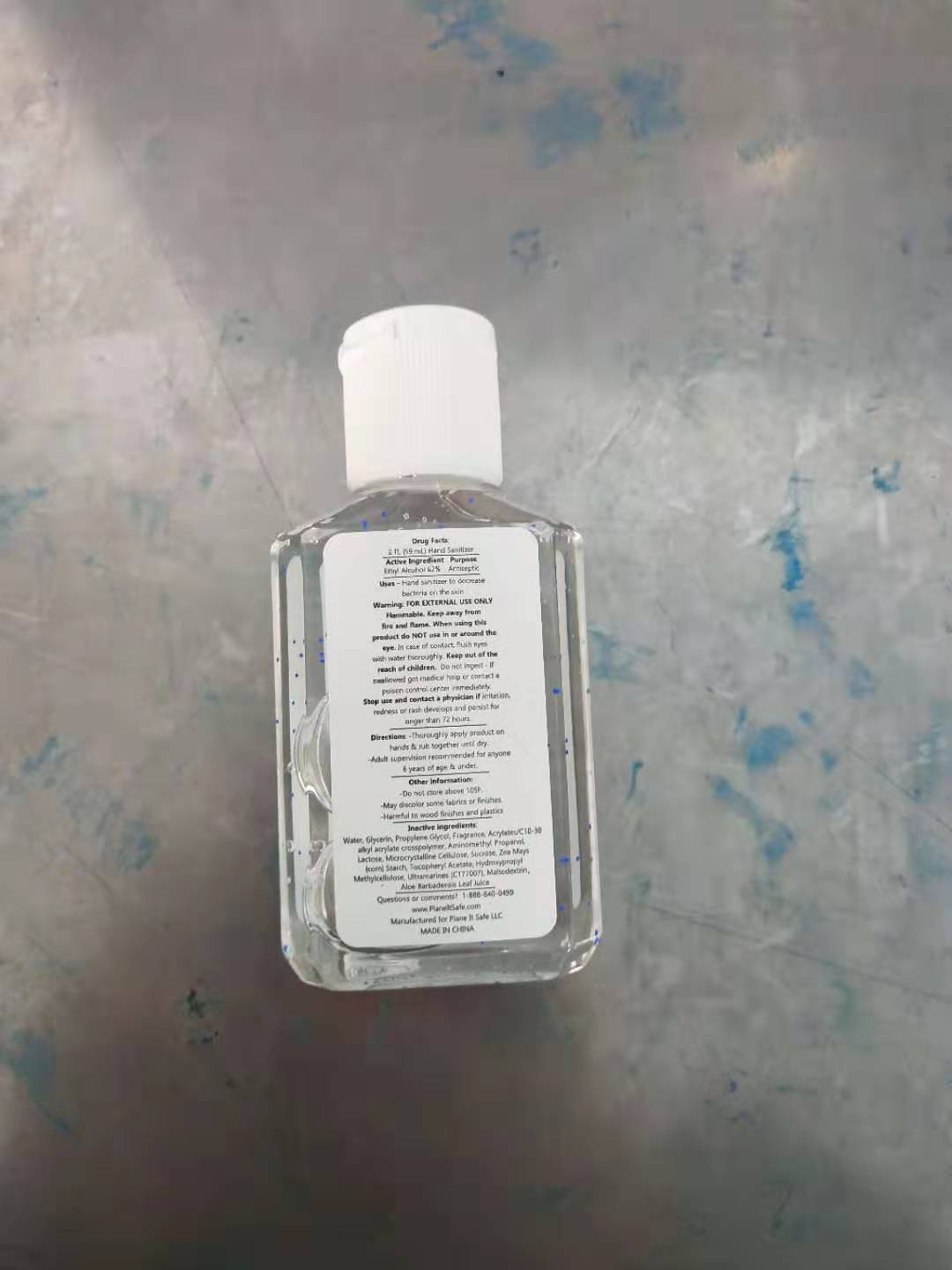 DRUG LABEL: Plane It Safe Hand Sanitizer
NDC: 72920-2001 | Form: GEL
Manufacturer: Plane It Safe LLC
Category: otc | Type: HUMAN OTC DRUG LABEL
Date: 20211224

ACTIVE INGREDIENTS: ALCOHOL 62 mL/100 mL
INACTIVE INGREDIENTS: WATER

Hand Sanitizer

Warnings: FOR EXTERNAL USE ONLY

Flammable- Keep away from heat and flames.

When using this product do NOT use in or around the eye. In case of contact, flush eyes with water thoroughly

Keep out of the reach of children. Do not ingest- If swallowed get medical help or contact a poison control center immediately.

STOP and ask a physician if irratition, redness or rash develop and persist for longer than 72 hours.

Directions:

-Thoroughly apply product on hands & rub together until dry.

-Adult supervision recommended for anyone 6 years of age & under.

Do not store above 105F

-May discolor some fabrics or finishes

-Harmful to wood finishes and plastics

Active Ingreditents

Ethyl Alcohol 62%

Keep out of the reach of children. Do not ingest and if swollowed get help or contact a poison control center immediately.

STOP USE

Stop use and contact a physician if irratitation redness or rash occur

Purpose

Purpose Antiseptic

DIRECTIONS:

Directions: Thoroughly apply the product on your hands and rub together until dry

INACTIVE SECTION

Inactive Ingredients: Water, Aloe Barbadensis Leaf Juice, Maltodextrin, Glycerin, Propylene Glycol, Acrylates/C10-30 Alkyl Acrylate Crosspolymer, Aminomethyl Propanol, Fragrance,Lactose,Microcrystalline Cellulose,Sucrose,Zea Mays(Corn) Starch,Tocopheryl Acetate,Hydroxypropyl Methylcellulose,Ultamarines(CI77007)

USES

Hand sanitizer to decrease bacteria on the skin